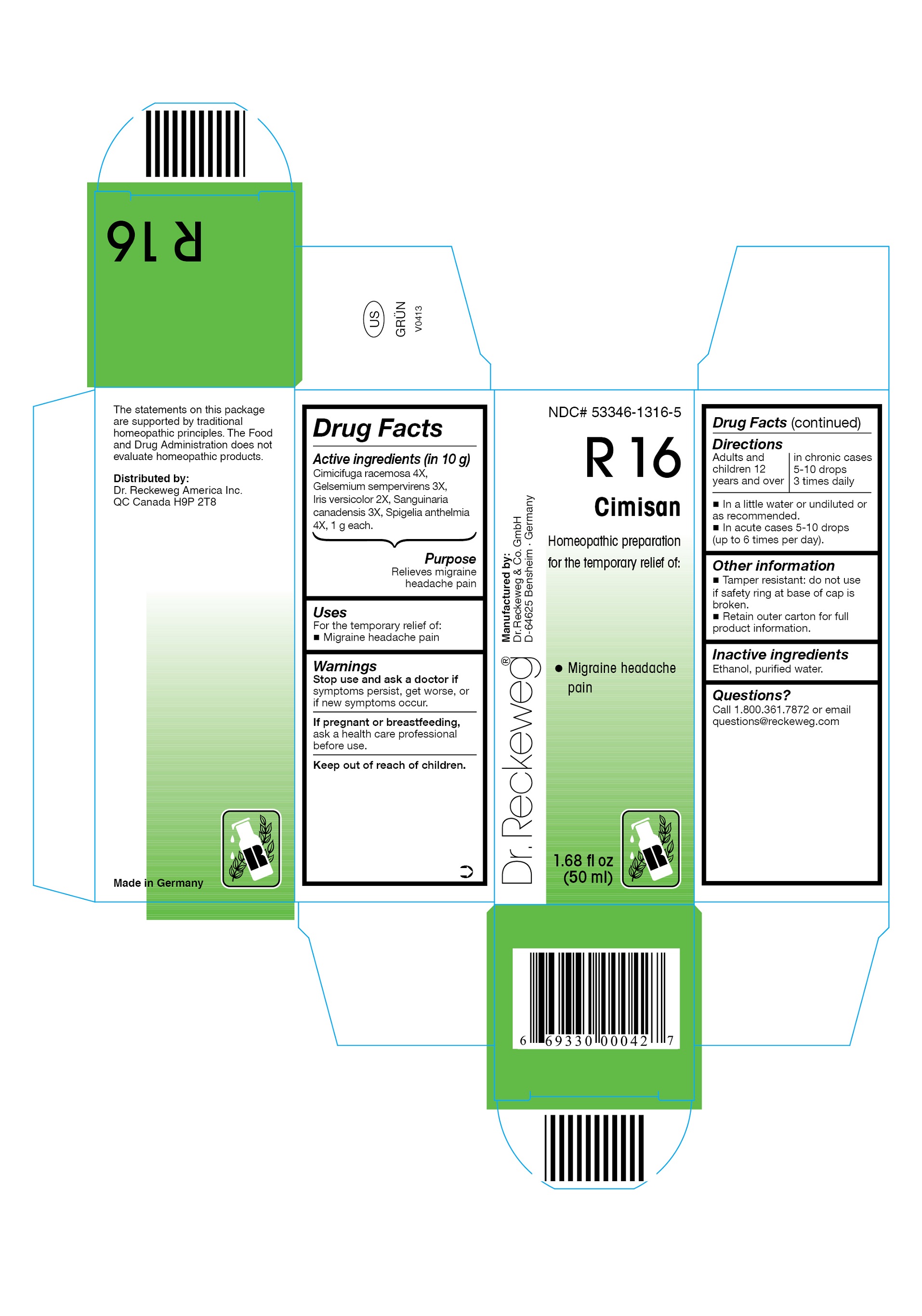 DRUG LABEL: DR. RECKEWEG R16 Cimisan
NDC: 53346-1316 | Form: LIQUID
Manufacturer: PHARMAZEUTISCHE FABRIK DR. RECKEWEG & CO
Category: homeopathic | Type: HUMAN OTC DRUG LABEL
Date: 20130404

ACTIVE INGREDIENTS: BLACK COHOSH 4 [hp_X]/50 mL; GELSEMIUM SEMPERVIRENS ROOT 3 [hp_X]/50 mL; IRIS VERSICOLOR ROOT 2 [hp_X]/50 mL; SANGUINARIA CANADENSIS ROOT 3 [hp_X]/50 mL; SPIGELIA ANTHELMIA 4 [hp_X]/50 mL
INACTIVE INGREDIENTS: ALCOHOL; WATER

DR. RECKEWEG R16 Cimisan

Active ingredients

Cimicifuga racemosa 4X, Gelsemium sempervirens 3X, Iris versicolor 2X, Sanguinaria canadensis 3X, Spigelia anthelmia 4X, 1 g each in 10 g.

Purpose

Relieves migraine headache pain

Uses

For the temporary relief of:

- Migraine headache pain

Warnings

Stop use and ask a doctor if symptoms persist, get worse, or if new symptoms occur.

PREGNANCY OR BREAST FEEDING

If pregnant or breastfeeding, ask a health care professional before use.

Keep out of reach of children.

Directions

Adults and children ≥ 12 years: acute cases: 5-10 drops (up to 6 times per day);

in chronic cases: 5-10 drops 3 times daily in a little water or undiluted or as recommended.

Other information

- Tamper resistant: do not use if safety ring at base of cap is broken.
- Retain outer carton for full product information.

Inactive ingredients

Ethanol, purified water.

Questions?
Call 1-800-361-7872 or email questions@reckeweg.com

PACKAGE LABEL

NDC# 53346-1316-5

Dr. Reckeweg R16 Cimisan

Homeopathic preparation for the temporary relief of:

- Migraine headache pain

Manufactured by:

Dr. Reckeweg Co. GmbH

D-64625 Bensheim

Germany

1.68 fl oz
(50 ml)